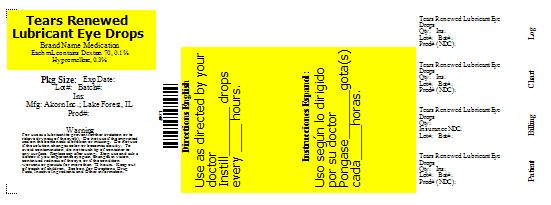 DRUG LABEL: Tears Renewed Lubricant
NDC: 68788-0039 | Form: SOLUTION
Manufacturer: Preferred Pharmaceuticals, Inc
Category: otc | Type: HUMAN OTC DRUG LABEL
Date: 20110506

ACTIVE INGREDIENTS: DEXTRAN 70 0.001 mL/1 mL; HYPROMELLOSES 0.003 mL/1 mL
INACTIVE INGREDIENTS: BENZALKONIUM CHLORIDE; POTASSIUM CHLORIDE; SODIUM BORATE; SODIUM CHLORIDE; BORIC ACID;  WATER; SODIUM CITRATE

Drug Facts

Active Ingredients

Dextran 70 (0.1%)...........................................................(Lubricant)

Hypromellose 2910 (0.3%)...............................................(Lubricant)

Uses

- for the temporary relief of burning and irritation of the eye and for use as a protectant against further irritation.
- for the temporary relief of discomfort due to minor irritations of the eye or to exposure to wind or sun.

Warnings

For external use only. Do not use: if this solution changes color or becomes cloudy or if you are sensitive to any ingredient in this product.

When using this product

- remove contact lenses before using
- to avoid contamination, do not touch tip
- replace cap after each use.

Stop use and ask a doctor if

- you feel eye pain
- changes in vision occur
- redness or irritation of the eye gets worse or lasts more than 72 hours.

If pregnant or breast-feeding,

ask a health professional before use.

Keep out of the reach of children.

If swallowed, get medical help or contact a Poison Control Center right away.

Directions

- Instill 1 or 2 drops in the affected eye(s) as needed.
- Store at room temperature.

INACTIVE INGREDIENT

Inactive Ingredients: Benzalkonium Chloride, Potassium Chloride, Disodium Chloride, Sodium Borate, Sodium Chloride, Boric Acid, Sterile Water, Purified Water, Sodium Chloride, and Sodium Citrate.

PRINCIPAL DISPLAY PANEL

Tears Renewed Lubricant Eye Drops

Relabeled By Preferred Pharmaceuticals, Inc
Anaheim, CA 92807

DOSAGE AND ADMINISTRATION

Use as directed by your doctor or pharmacist